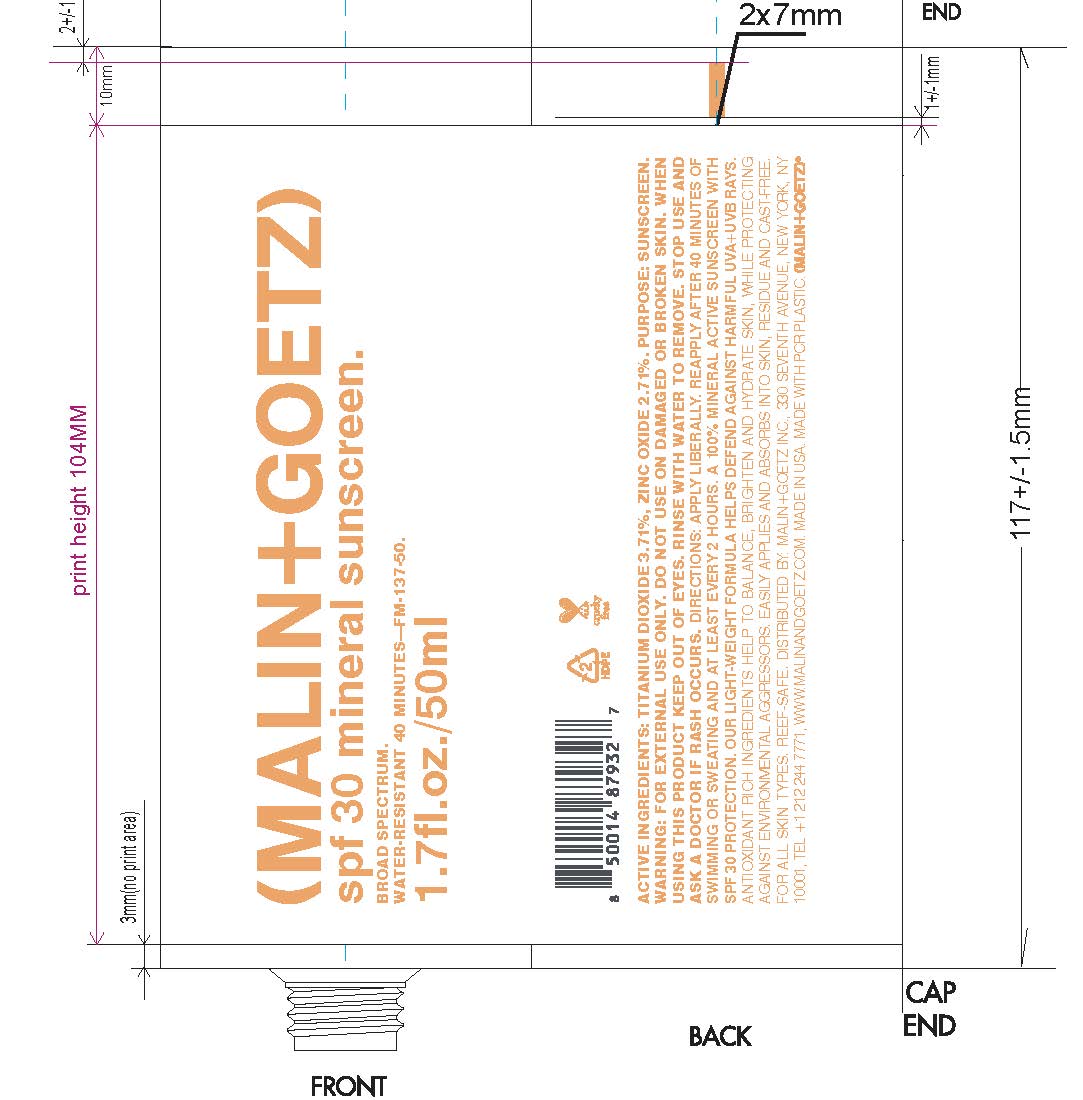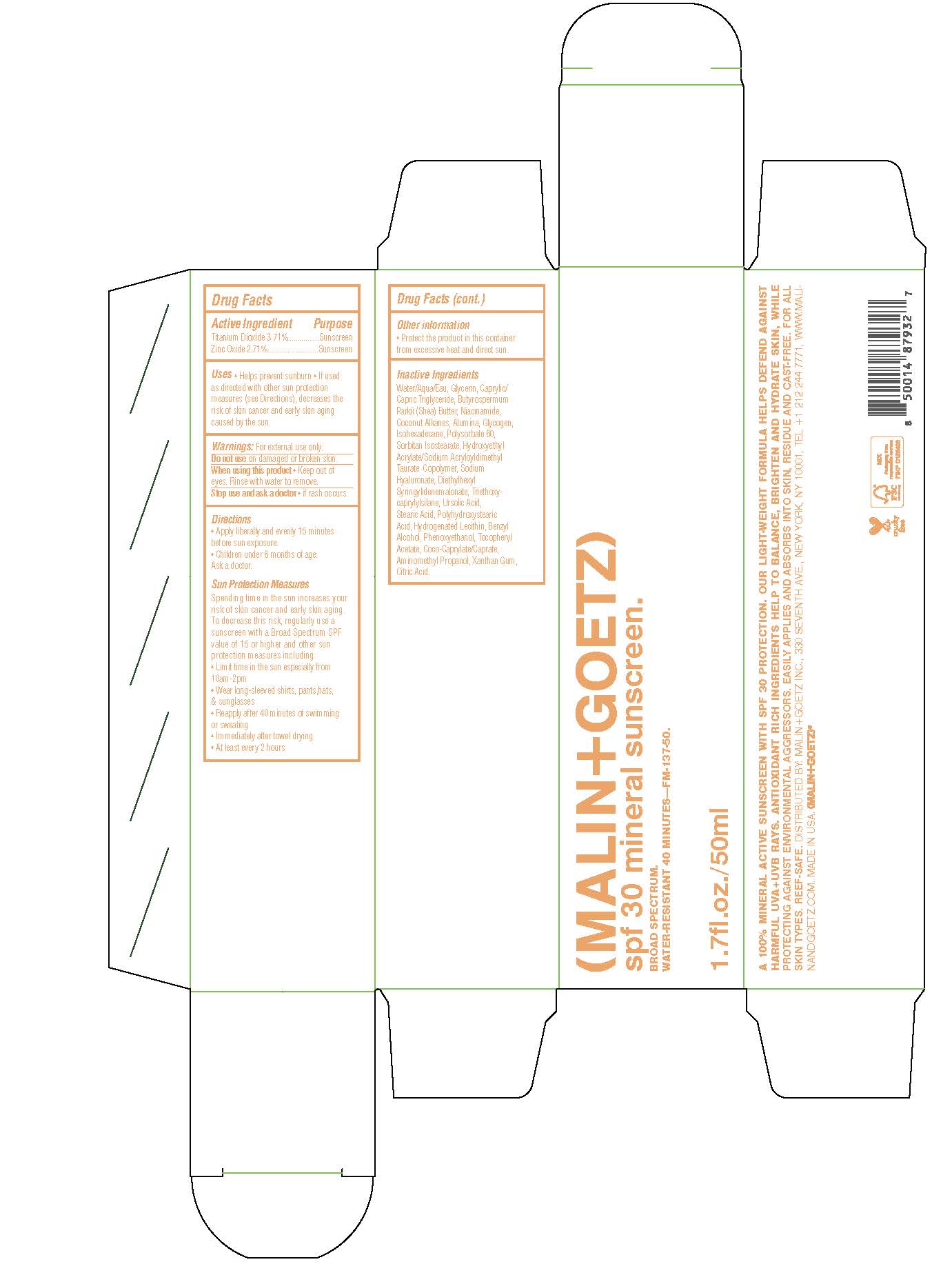 DRUG LABEL: spf 30 mineral Sunscreen
NDC: 53634-128 | Form: CREAM
Manufacturer: Malin and Goetz Inc
Category: otc | Type: HUMAN OTC DRUG LABEL
Date: 20251001

ACTIVE INGREDIENTS: TITANIUM DIOXIDE 3.71 g/100 mL; ZINC OXIDE 2.71 g/100 mL
INACTIVE INGREDIENTS: DIETHYLHEXYL SYRINGYLIDENEMALONATE; BENZYL ALCOHOL; PHENOXYETHANOL; SHEA BUTTER; POLYSORBATE 60; SORBITAN ISOSTEARATE; URSOLIC ACID; STEARIC ACID; HYDROGENATED SOYBEAN LECITHIN; GLYCERIN; COCONUT ALKANES; XANTHAN GUM; CITRIC ACID MONOHYDRATE; ISOHEXADECANE; WATER; ALUMINUM OXIDE; HYDROXYETHYL ACRYLATE/SODIUM ACRYLOYLDIMETHYL TAURATE COPOLYMER (45000 MPA.S AT 1%); HYALURONATE SODIUM; POLYHYDROXYSTEARIC ACID (2300 MW); .ALPHA.-TOCOPHEROL ACETATE; COCO-CAPRYLATE/CAPRATE; AMINOMETHYLPROPANOL; MEDIUM-CHAIN TRIGLYCERIDES; NIACINAMIDE; GLYCOGEN; TRIETHOXYCAPRYLYLSILANE

(Malin+Goetz) SPF 30 mineral Sunscreen

Active Ingredient Purpose

Titanium Dioxide 3.71% Sunscreen

Zinc Oxide 2.71% Sunscreen

Uses

- Helps prevent sunburn
- If used as directed with other sun protection measures (see directions), decreases the risk of skin cancer and early skin aging caused by the sun

Keep out of reach of children

Stop use and ask a doctor

- if rash occurs

Warnings: For external use only

Do not use on damaged or broken skin

When using this product

- Keep out of eyes. RInse with water to remove

Directions

- Apply liberally and evenly 15 minutes before sun exposure
- Children under 6 months of age: ask a doctor

Sun Protection Measures

Spending time in the sun increases your risk of skin cancer and early skin aging. To decrease this risk, regularly use a

sunscreen with a Broad-Spectrum SPF value of 15 or higher and other sun protection measures including:

limit your time in the sun, especially from 10a.m. – 2 p.m.

- wear long-sleeved shirts, pants, hats, and sunglasses
- reapply after 40 minutes of swimming or sweating
- Immediately after towel drying
- At least every 2 hours

Inactive ingredients

Water/Aqua/Eau, Glycerin, Caprylic/Capric Triglyceride, Butyrospermum Parkii (Shea) Butter, Niacinamide, Coconut Alkanes, Alumina, Glycogen, Isohexadecane, Polysorbate 60, Sorbitan Isostearate, Hydroxyethyl Acrylate/Sodium Acryloyldimethyl Taurate Copolymer, Sodium Hyaluronate, Diethylhexyl Syringlidenemalonate, Triethoxycaprylylsilane, Ursolic Acid, Stearic Acid, Polyhydroxystearic Acid, hydrogenated Lecithin, Benzyl Alcohol, Phenoxyethanol, Tocopheryl Acetate, Coco-Caprylate/Caprate, Aminomethyl Propanol, Xanthan Gum, Citric Acid.

PACKAGE LABEL

(Malin+Goetz)

spf 30 mineral sunscreen

Broad Spectrum

Water-Resistant 40 minutes

1.7 fl.oz./50 ml